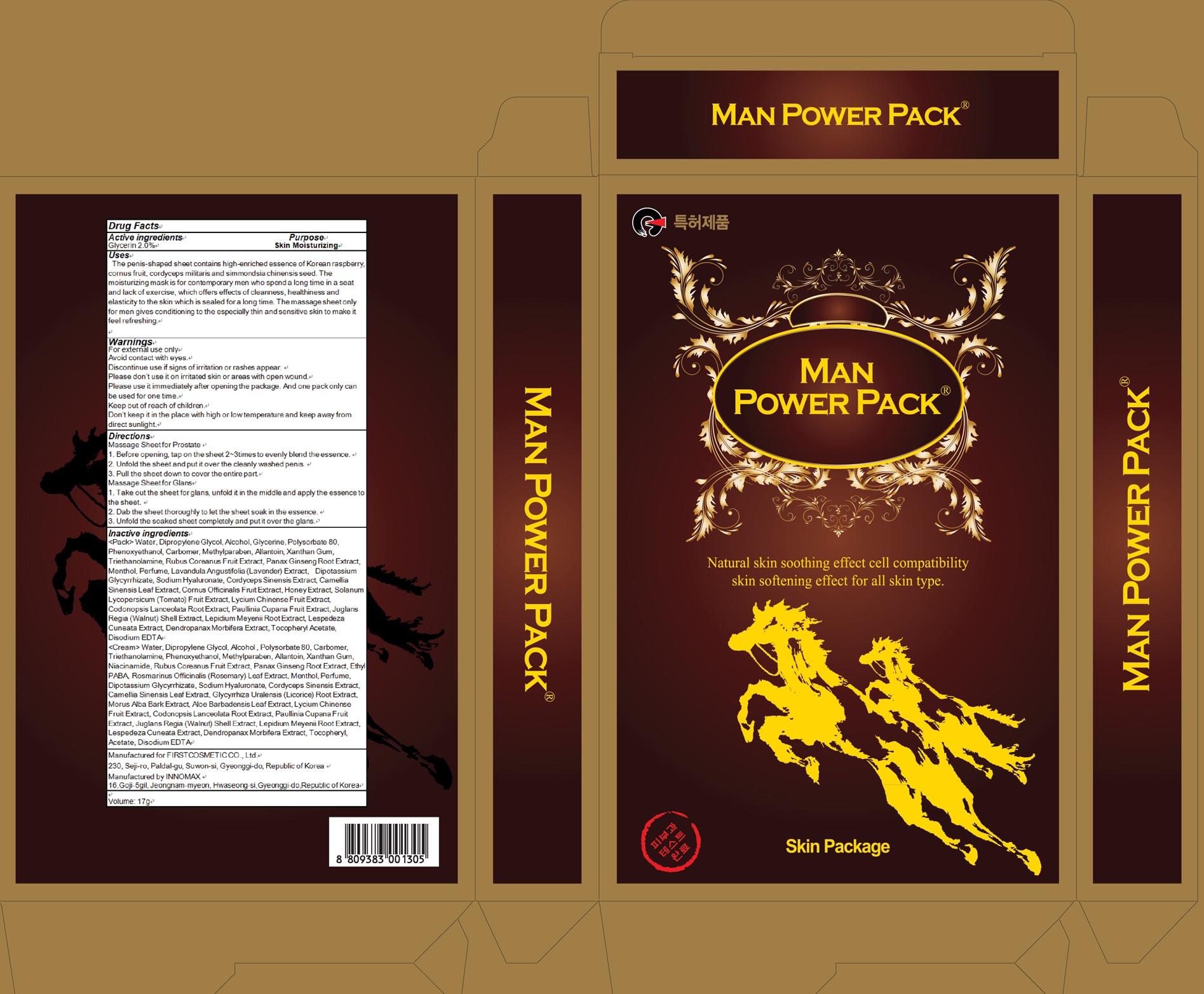 DRUG LABEL: Man Power Pack
NDC: 71635-060 | Form: PATCH
Manufacturer: First Cosmetic Co., Ltd
Category: otc | Type: HUMAN OTC DRUG LABEL
Date: 20171020

ACTIVE INGREDIENTS: Glycerin 0.34 g/17 g
INACTIVE INGREDIENTS: Water; Dipropylene Glycol

ACTIVE INGREDIENT

Active ingredients: Glycerin 2.0%

INACTIVE INGREDIENT

Inactive ingredients:

<Pack> Water, Dipropylene Glycol, Alcohol, Glycerine, Polysorbate 80, Phenoxyethanol, Carbomer, Methylparaben, Allantoin, Xanthan Gum, Triethanolamine, Rubus Coreanus Fruit Extract, Panax Ginseng Root Extract, Menthol, Perfume, Lavandula Angustifolia (Lavender) Extract, Dipotassium Glycyrrhizate, Sodium Hyaluronate, Cordyceps Sinensis Extract, Camellia Sinensis Leaf Extract, Cornus Officinalis Fruit Extract, Honey Extract, Solanum Lycopersicum (Tomato) Fruit Extract, Lycium Chinense Fruit Extract, Codonopsis Lanceolata Root Extract, Paullinia Cupana Fruit Extract, Juglans Regia (Walnut) Shell Extract, Lepidium Meyenii Root Extract, Lespedeza Cuneata Extract, Dendropanax Morbifera Extract, Tocopheryl Acetate, Disodium EDTA

<Cream> Water, Dipropylene Glycol, Alcohol , Polysorbate 80, Carbomer, Triethanolamine, Phenoxyethanol, Methylparaben, Allantoin, Xanthan Gum, Niacinamide, Rubus Coreanus Fruit Extract, Panax Ginseng Root Extract, Ethyl PABA, Rosmarinus Officinalis (Rosemary) Leaf Extract, Menthol, Perfume, Dipotassium Glycyrrhizate, Sodium Hyaluronate, Cordyceps Sinensis Extract, Camellia Sinensis Leaf Extract, Glycyrrhiza Uralensis (Licorice) Root Extract, Morus Alba Bark Extract, Aloe Barbadensis Leaf Extract, Lycium Chinense Fruit Extract, Codonopsis Lanceolata Root Extract, Paullinia Cupana Fruit Extract, Juglans Regia (Walnut) Shell Extract, Lepidium Meyenii Root Extract, Lespedeza Cuneata Extract, Dendropanax Morbifera Extract, Tocopheryl, Acetate, Disodium EDTA

PURPOSE

Purpose: Skin Moisturizing

WARNINGS

Warnings: For external use only Avoid contact with eyes. Discontinue use if signs of irritation or rashes appear. Please don’t use it on irritated skin or areas with open wound. Please use it immediately after opening the package. And one pack only can be used for one time. Keep out of reach of children. Don’t keep it in the place with high or low temperature and keep away from direct sunlight.

KEEP OUT OF REACH OF CHILDREN

Uses

Uses: The penis-shaped sheet contains high-enriched essence of Korean raspberry, cornus fruit, cordyceps militaris and simmondsia chinensis seed. The moisturizing mask is for contemporary men who spend a long time in a seat and lack of exercise, which offers effects of cleanness, healthiness and elasticity to the skin which is sealed for a long time. The massage sheet only for men gives conditioning to the especially thin and sensitive skin to make it feel refreshing.

Directions

Massage Sheet for Prostate 1. Before opening, tap on the sheet 2~3times to evenly blend the essence. 2. Unfold the sheet and put it over the cleanly washed penis. 3. Pull the sheet down to cover the entire part.

Massage Sheet for Glans 1. Take out the sheet for glans, unfold it in the middle and apply the essence to the sheet. 2. Dab the sheet thoroughly to let the sheet soak in the essence. 3. Unfold the soaked sheet completely and put it over the glans.